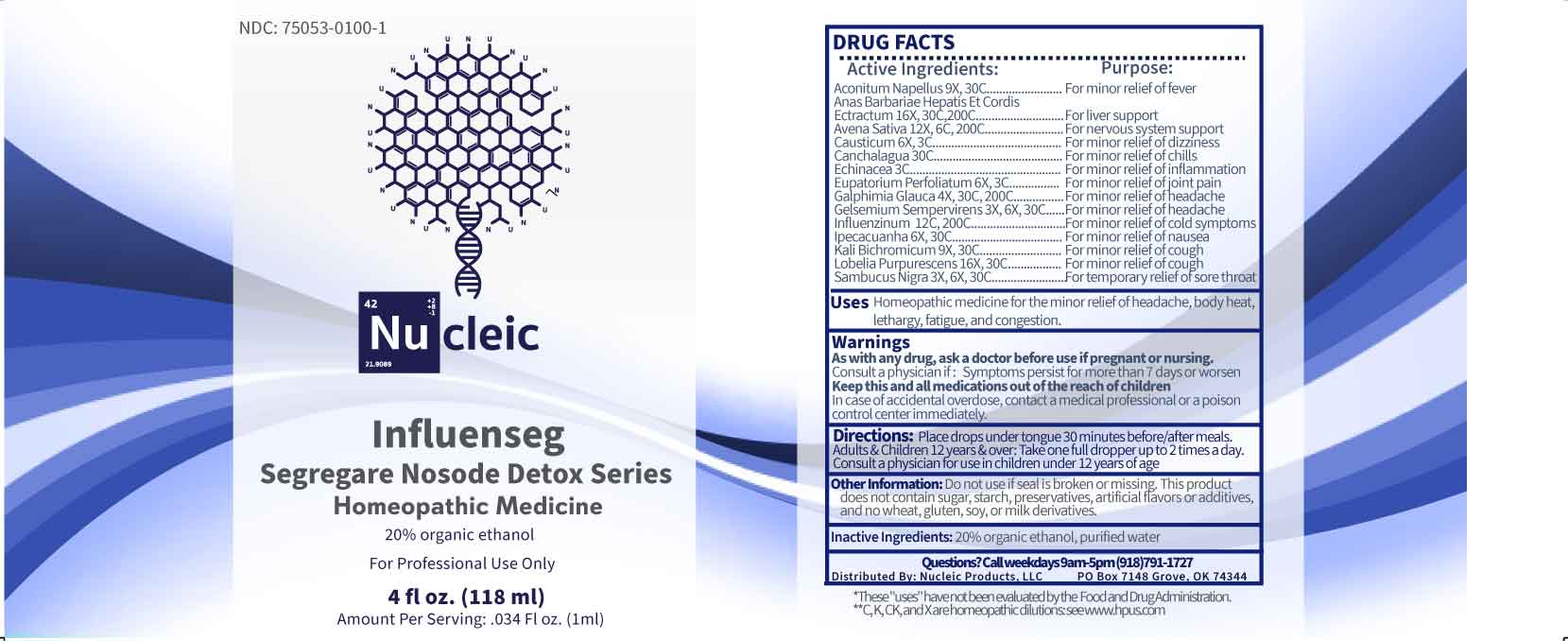 DRUG LABEL: Influenseg
NDC: 75053-0100 | Form: LIQUID
Manufacturer: Nucleic Products, LLC
Category: homeopathic | Type: HUMAN OTC DRUG LABEL
Date: 20260227

ACTIVE INGREDIENTS: GELSEMIUM SEMPERVIRENS ROOT 3 [hp_X]/1 mL; SAMBUCUS NIGRA FLOWERING TOP 3 [hp_X]/1 mL; GALPHIMIA GLAUCA FLOWERING TOP 4 [hp_X]/1 mL; CAUSTICUM 6 [hp_X]/1 mL; EUPATORIUM PERFOLIATUM FLOWERING TOP 6 [hp_X]/1 mL; IPECAC 6 [hp_X]/1 mL; ACONITUM NAPELLUS WHOLE 9 [hp_X]/1 mL; POTASSIUM DICHROMATE 9 [hp_X]/1 mL; AVENA SATIVA FLOWERING TOP 12 [hp_X]/1 mL; INFLUENZA A VIRUS A/VICTORIA/4897/2022 IVR-238 (H1N1) ANTIGEN (FORMALDEHYDE INACTIVATED) 12 [hp_C]/1 mL; INFLUENZA A VIRUS A/THAILAND/8/2022 IVR-237 (H3N2) ANTIGEN (FORMALDEHYDE INACTIVATED) 12 [hp_C]/1 mL; INFLUENZA B VIRUS B/AUSTRIA/1359417/2021 BVR-26 WHOLE 12 [hp_C]/1 mL; INFLUENZA B VIRUS B/PHUKET/3073/2013 BVR-1B WHOLE 12 [hp_C]/1 mL; PRATIA PURPURASCENS 16 [hp_X]/1 mL; CAIRINA MOSCHATA HEART/LIVER AUTOLYSATE 16 [hp_X]/1 mL; ECHINACEA ANGUSTIFOLIA WHOLE 3 [hp_C]/1 mL; ZELTNERA VENUSTA WHOLE FLOWERING 30 [hp_C]/1 mL
INACTIVE INGREDIENTS: WATER; ALCOHOL

DRUG FACTS:

ACTIVE INGREDIENTS:

Aconitum Napellus 9X, 30C, Anas Barbariae, Hepatis ET Cordis Extractum 16X, 30C, 200C, Avena Sativa 12X, 6C, 200C, Causticum 6X, 3C, Canchalagua 30C, Echinacea 3C, Eupatorium Perfoliatum 6X, 3C, Galphimia Glauca 4X, 30C, 200C, Gelsemium Sempervirens 3X, 6X, 30C, Influenzinum 12X, 200C, Ipecacuanha 6X, 30C, Kali Bichromicum 9X, 30C, Lobelia Purpurescens 16X, 30C, Sambucus Nigra 3X, 6X, 30C.

PURPOSE:

Aconitum Napellus – For minor relief of fever, Anas Barbariae, Hepatis ET Cordis Extractum – For liver support, Avena Sativa – For nervous system support, Causticum – For minor relief of dizziness, Canchalagua – For minor relief of chills, Echinacea – For minor relief of inflammation, Eupatorium Perfoliatum – For minor relief of joint pain, Galphimia Glauca – for minor relief of headache, Gelsemium Sempervirens – for minor relief of headache, Influenzinum – For minor relief of cold symptoms, Ipecacuanha – For minor relief of nausea, Kali Bichromicum – For minor relief of cough, Lobelia Purpurescens – for minor relief of cough, Sambucus Nigra – For temporary relief of sore throat

USES:

Homeopathic medicine for the minor relief of headache, body heat, lethargy, fatigue and congestion.

These "uses" have not been evaluated by the Food and Drug Administration.

WARNINGS:

As with any drug, ask a doctor before use if pregnant or nursing.

Consult a physician if: Symptoms persist for more than 7 days or worsen

Keep this and all medications out of the reach of children.

In case of accidental overdose, contact a medical professional or a poison control center immediately.

Do not use if seal is broken or missing.

This Product does not contain sugar, starch, preservatives, artificial flavors or additives, and no wheat, gluten, soy, or milk derivatives.

KEEP OUT OF REACH OF CHILDREN:

In case of accidental overdose, contact a medical professional or a poison control center immediately.

DIRECTIONS:

Place drops under tongue 30 minutes before/after meals. Adults & Children 12 years & over: Take one full dropper up to 2 times a day.

Consult a physician for use in children under 12 years of age.

INACTIVE INGREDIENTS:

20% organic ethanol, purified water

QUESTIONS:

Distributed by:
Nucleic Products, LLC

PO Box 7148

Grove, OK 74344

Call weekdays 9am-5pm (918)791-1727

PACKAGE LABEL DISPLAY:

NDC: 75053-0100-1

Nu cleic

Influenseg

Segregare Nosode Detox Series

Homeopathic Medicine

For Professional Use Only

4 fl oz. (118 ml)